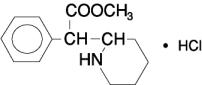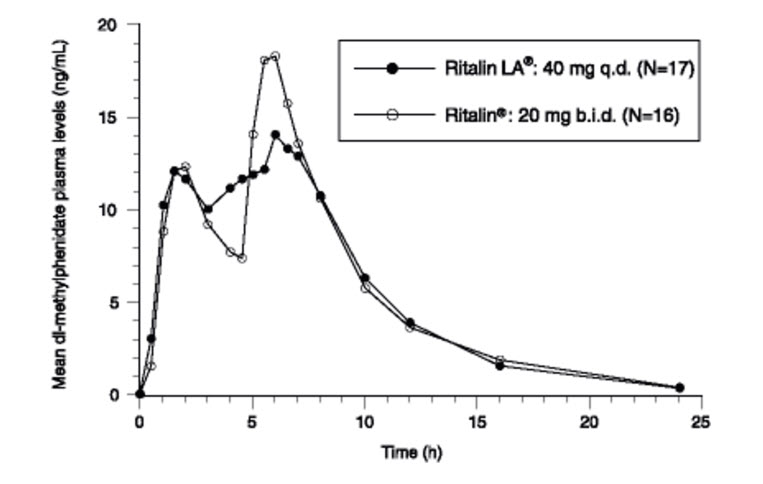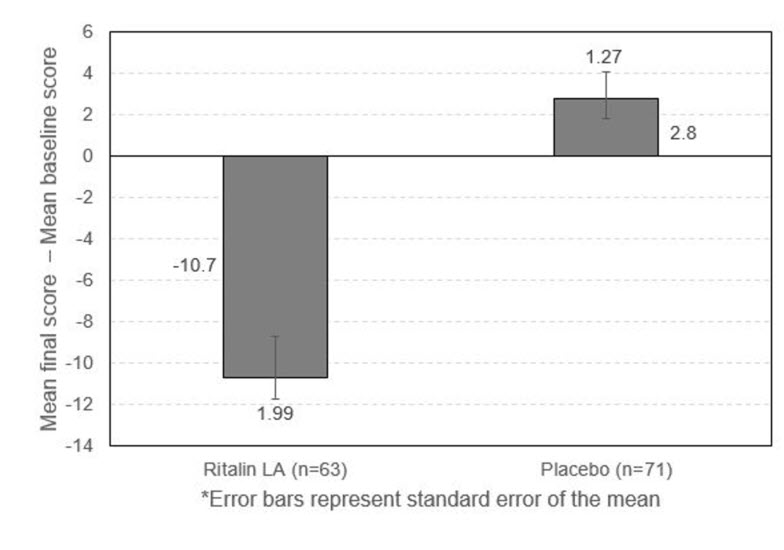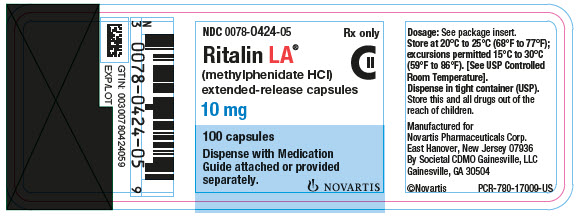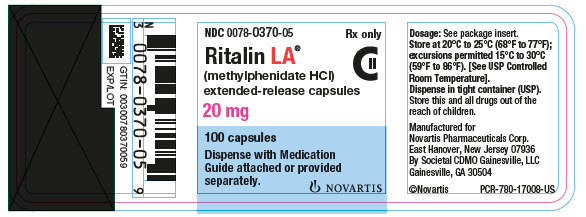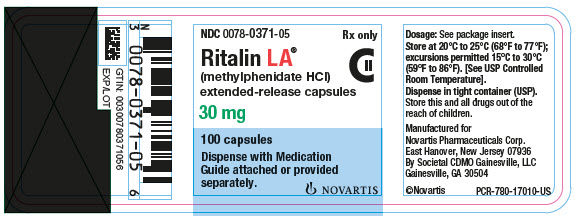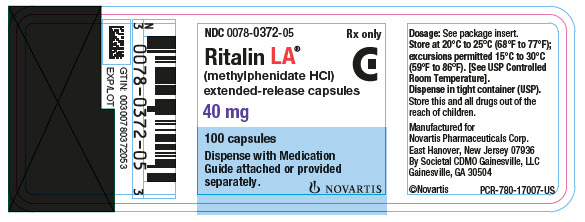 DRUG LABEL: Ritalin
NDC: 0078-0370 | Form: CAPSULE, EXTENDED RELEASE
Manufacturer: Novartis Pharmaceuticals Corporation
Category: prescription | Type: HUMAN PRESCRIPTION DRUG LABEL
Date: 20250923
DEA Schedule: CII

ACTIVE INGREDIENTS: METHYLPHENIDATE HYDROCHLORIDE 20 mg/1 1
INACTIVE INGREDIENTS: GELATIN, UNSPECIFIED; POLYETHYLENE GLYCOL, UNSPECIFIED; DEXTROSE, UNSPECIFIED FORM; TALC; TITANIUM DIOXIDE; TRIETHYL CITRATE

HIGHLIGHTS OF PRESCRIBING INFORMATION

These highlights do not include all the information needed to use RITALIN LA safely and effectively. See full prescribing information for RITALIN LA.
RITALIN LA® (methylphenidate hydrochloride) extended-release capsules for oral use, CII
Initial U.S. Approval: 1955

RECENT MAJOR CHANGES

Indications and Usage (1) 09/2025

Warnings and Precautions (5.7) 09/2025

WARNING: ABUSE, MISUSE, AND ADDICTION

See full prescribing information for complete boxed warning.

Ritalin LA has a high potential for abuse and misuse, which can lead to the development of a substance use disorder, including addiction. Misuse and abuse of CNS stimulants, including Ritalin LA, can result in overdose and death (5.1, 9.2, 10).

- Before prescribing Ritalin LA, assess each patient’s risk for abuse, misuse, and addiction.
- Educate patients and their families about these risks, proper storage of the drug, and proper disposal of any unused drug.
- Throughout treatment, reassess each patient’s risk and frequently monitor for signs and symptoms of abuse, misuse, and addiction.

1 INDICATIONS AND USAGE

Ritalin LA is a central nervous system (CNS) stimulant indicated for the treatment of Attention Deficit Hyperactivity Disorder (ADHD) in pediatric patients 6 to 12 years of age (1).

Limitations of Use

The use of Ritalin LA is not recommended in pediatric patients younger than 6 years of age because they had higher plasma exposure and a higher incidence of adverse reactions (e.g., weight loss) than patients 6 years and older at the same dosage (5.7, 8.4).

2 DOSAGE AND ADMINISTRATION

- Administer orally once daily in the morning (2.2).
- Capsules may be swallowed whole or opened and the entire contents sprinkled on applesauce (2.2).
- Should not be crushed, chewed, or divided (2.2).
- Patients new to methylphenidate: Start at 20 mg daily, titrating the dose weekly in 10-mg increments. Doses above 60 mg daily are not recommended (2.3).
- For patients currently using Ritalin: Dosage is based on current dose regimen (2.4).
- If switching from other methylphenidate products, discontinue treatment and titrate with Ritalin LA (2.4).

3 DOSAGE FORMS AND STRENGTHS

Extended-release capsules: 10 mg, 20 mg, 30 mg, and 40 mg (3).

4 CONTRAINDICATIONS

- Known hypersensitivity to methylphenidate or product components (4).
- Concurrent treatment with a monoamine oxidase inhibitor (MAOI) or use of an MAOI within the preceding 14 days (4).

5 WARNINGS AND PRECAUTIONS

- Risks to Patients with Serious Cardiac Disease: Avoid use in patients with known structural cardiac abnormalities, cardiomyopathy, serious cardiac rhythm arrhythmias, coronary artery disease, or other serious cardiac disease (5.2).
- Increased Blood Pressure and Heart Rate: Monitor blood pressure and pulse (5.3).
- Psychiatric Adverse Reactions: Prior to initiating Ritalin LA, screen patients for risk factors for developing a manic episode. If new psychotic or manic symptoms occur, consider discontinuing Ritalin LA (5.4).
- Priapism: If abnormally sustained or frequent and painful erections occur, patients should seek immediate medical attention (5.5).
- Peripheral Vasculopathy, including Raynaud’s Phenomenon: Careful observation for digital changes is necessary during Ritalin LA treatment. Further clinical evaluation (e.g., rheumatology referral) may be appropriate for patients who develop signs or symptoms of peripheral vasculopathy (5.6).
- Long-Term Suppression of Growth in Pediatric Patients: Closely monitor growth (height and weight) in pediatric patients. Pediatric patients not growing or gaining height or weight as expected may need to have their treatment interrupted (5.7).
- Acute Angle Closure Glaucoma: Ritalin LA-treated patients considered at risk for acute angle closure glaucoma (e.g., patients with significant hyperopia) should be evaluated by an ophthalmologist (5.8).
- Increased Intraocular Pressure (IOP) and Glaucoma: Prescribe Ritalin LA to patients with open-angle glaucoma or abnormally increased IOP only if the benefit of treatment is considered to outweigh the risk. Closely monitor patients with a history of abnormally increased IOP or open angle glaucoma (5.9).
- Motor and Verbal Tics, and Worsening of Tourette’s Syndrome: Before initiating Ritalin LA, assess the family history and clinically evaluate patients for tics or Tourette’s syndrome. Regularly monitor patients for the emergence or worsening of tics or Tourette’s syndrome. Discontinue treatment if clinically appropriate (5.10).

6 ADVERSE REACTIONS

Most common adverse reactions (greater than 5% during incidence) were headache, insomnia, upper abdominal pain, decreased appetite, and anorexia (6).

To report SUSPECTED ADVERSE REACTIONS, contact Novartis Pharmaceuticals Corporation at 1-888-669-6682 or FDA at 1-800-FDA-1088 or www.fda.gov/medwatch.

7 DRUG INTERACTIONS

- Antihypertensive Drugs: Monitor blood pressure and heart. Adjust dosage of antihypertensive drug as needed (7.1).

FULL PRESCRIBING INFORMATION

WARNING: ABUSE, MISUSE, AND ADDICTION

Ritalin LA has a high potential for abuse and misuse, which can lead to the development of a substance use disorder, including addiction. Misuse and abuse of CNS stimulants, including Ritalin LA, can result in overdose and death [see Overdosage (10)], and this risk is increased with higher doses or unapproved methods of administration, such as snorting or injection.

Before prescribing Ritalin LA, assess each patient’s risk for abuse, misuse, and addiction. Educate patients and their families about these risks, proper storage of the drug, and proper disposal of any unused drug. Throughout Ritalin LA treatment, reassess each patient’s risk of abuse, misuse, and addiction and frequently monitor for signs and symptoms of abuse, misuse, and addiction [see Warnings and Precautions (5.1), Drug Abuse and Dependence (9.2)].

1 INDICATIONS AND USAGE

Ritalin LA® is indicated for the treatment of Attention Deficit Hyperactivity Disorder (ADHD), in pediatric patients 6 to 12 years of age [see Clinical Studies (14)].

Limitations of Use

The use of Ritalin LA is not recommended in pediatric patients younger than 6 years of age because they had higher plasma exposure and a higher incidence of adverse reactions (e.g., weight loss) than patients 6 years and older at the same dosage [see Warnings and Precautions (5.7), Use in Specific Populations (8.4)].

2 DOSAGE AND ADMINISTRATION

2.1 Pretreatment Screening

Prior to treating patients with Ritalin LA, assess:

- for the presence of cardiac disease (i.e., perform a careful history, family history of sudden death or ventricular arrhythmia, and physical exam) [see Warnings and Precautions (5.2)].
- the family history and clinically evaluate patients for motor or verbal tics or Tourette’s syndrome before initiating Ritalin LA [see Warnings and Precautions (5.10)].

2.2 General Dosing Information

The recommended starting dose for Ritalin LA is 20 mg once daily. Increase dosage gradually, in increments of 10 mg weekly. Daily dosage above 60 mg is not recommended. When a lower initial dose is appropriate, patients may begin treatment with 10 mg.

Administer Ritalin LA orally once daily in the morning. Ritalin LA may be swallowed as whole capsules or may be administered by sprinkling the capsule contents on a small amount of applesauce (see specific instructions below). Ritalin LA and/or their contents should not be crushed, chewed, or divided.

The capsules may be carefully opened and the beads sprinkled over a spoonful of applesauce. The applesauce should not be warm because it could affect the modified release properties of this formulation. The mixture of drug and applesauce should be consumed immediately in its entirety. The drug and applesauce mixture should not be stored for future use.

2.3 Patients Currently Using Ritalin

The recommended dose of Ritalin LA for patients currently taking Ritalin twice daily is provided below in Table 1.

Table 1: Recommended Dose Conversion from Ritalin
Previous Ritalin dose | Recommended Ritalin LA dose
5 mg Ritalin twice daily | 10 mg once daily
10 mg Ritalin twice daily | 20 mg once daily
15 mg Ritalin twice daily | 30 mg once daily
20 mg Ritalin twice daily | 40 mg once daily
30 mg Ritalin twice daily | 60 mg once daily

2.4 Switching from Other Methylphenidate Products

If switching from other methylphenidate products, discontinue that treatment, and titrate with Ritalin LA using the titration schedule.

Do not substitute for other methylphenidate products on a milligram-per-milligram basis, because different methylphenidate base compositions and differing pharmacokinetic profiles [see Description (11), Clinical Pharmacology (12.3)].

Clinical judgment should be used when selecting the starting dose. Daily dosage above 60 mg is not recommended.

2.5 Dosage Reduction and Discontinuation

If paradoxical worsening of symptoms or other adverse reactions occur, reduce the dosage, or, if necessary, discontinue Ritalin LA. If improvement is not observed after appropriate dosage adjustment over a one-month period, the drug should be discontinued.

3 DOSAGE FORMS AND STRENGTHS

- 10 mg extended-release capsules white/light brown, (imprinted "NVR R10")
- 20 mg extended-release capsules white, (imprinted "NVR R20")
- 30 mg extended-release capsules yellow, (imprinted "NVR R30")
- 40 mg extended-release capsules light brown, (imprinted "NVR R40")

4 CONTRAINDICATIONS

- Hypersensitivity to methylphenidate or other components of Ritalin LA. Hypersensitivity reactions, such as angioedema and anaphylactic reactions, have been reported in patients treated with methylphenidate [see Adverse Reactions (6.1)].
- Concomitant treatment with monoamine oxidase inhibitors (MAOIs), or within 14 days following discontinuation of treatment with an MAOI, because of the risk of hypertensive crises [see Drug Interactions (7.1)].

5 WARNINGS AND PRECAUTIONS

5.1 Abuse, Misuse, and Addiction

Ritalin LA has a high potential for abuse and misuse. The use of Ritalin LA exposes individuals to the risks of abuse and misuse, which can lead to the development of a substance use disorder, including addiction. Ritalin LA can be diverted for non-medical use into illicit channels or distribution [see Drug Abuse and Dependence (9.2)]. Misuse and abuse of CNS stimulants, including Ritalin LA, can result in overdose and death [see Overdosage (10)], and this risk is increased with higher doses or unapproved methods of administration, such as snorting or injection.

Before prescribing Ritalin LA, assess each patient’s risk for abuse, misuse, and addiction. Educate patients and their families about these risks and proper disposal of any unused drug. Advise patients to store Ritalin LA in a safe place, preferably locked, and instruct patients to not give Ritalin LA to anyone else. Throughout Ritalin LA treatment, reassess each patient’s risk of abuse, misuse, and addiction and frequently monitor for signs and symptoms of abuse, misuse, and addiction.

5.2 Risks to Patients with Serious Cardiac Disease

Sudden death has been reported in patients with structural cardiac abnormalities or other serious cardiac disease who are treated with CNS stimulants at the recommended ADHD dosage.

Avoid Ritalin LA use in patients with known structural cardiac abnormalities, cardiomyopathy, serious cardiac arrhythmia, coronary artery disease, or other serious cardiac disease.

5.3 Increased Blood Pressure and Heart Rate

CNS stimulants cause an increase in blood pressure (mean increase approximately 2 to 4 mmHg) and heart rate (mean increase approximately 3 to 6 beats per minute). Some patients may have larger increases. Monitor all Ritalin LA-treated patients for hypertension and tachycardia.

5.4 Psychiatric Adverse Reactions

Exacerbation of Preexisting Psychosis

CNS stimulants may exacerbate symptoms of behavior disturbance and thought disorder in patients with a preexisting psychotic disorder.

Induction of a Manic Episode in Patients with Bipolar Disorder

CNS stimulants may induce a manic or mixed mood episode in patients. Prior to initiating Ritalin LA treatment, screen patients for risk factors for developing a manic episode (e.g., comorbid or history of depressive symptoms or a family history of suicide, bipolar disorder, or depression).

New Psychotic or Manic Symptoms

CNS stimulants, at the recommended dosage, may cause psychotic or manic symptoms (e.g., hallucinations, delusional thinking, or mania) in patients without a prior history of psychotic illness or mania. In a pooled analysis of multiple short-term, placebo-controlled studies of CNS stimulants, psychotic or manic symptoms occurred in approximately 0.1% of CNS stimulant-treated patients, compared to 0% of placebo-treated patients. If such symptoms occur, consider discontinuing Ritalin LA.

5.5 Priapism

Prolonged and painful erections, sometimes requiring surgical intervention, have been reported with methylphenidate use in both adult and pediatric male patients. Although priapism was not reported with methylphenidate initiation, it developed after some time on methylphenidate, often subsequent to an increase in dosage. Priapism also occurred during methylphenidate withdrawal (drug holidays or during discontinuation).

Ritalin LA-treated patients who develop abnormally sustained or frequent and painful erections should seek immediate medical attention.

5.6 Peripheral Vasculopathy, Including Raynaud’s Phenomenon

CNS stimulants, including Ritalin LA, used to treat ADHD are associated with peripheral vasculopathy, including Raynaud’s phenomenon. Signs and symptoms are usually intermittent and mild; however, sequelae have included digital ulceration and/or soft tissue breakdown. Effects of peripheral vasculopathy, including Raynaud’s phenomenon were observed in post-marketing reports and at the therapeutic dosage of CNS stimulants in all age groups throughout the course of treatment. Signs and symptoms generally improved after dosage reduction or the CNS stimulant.

Careful observation for digital changes is necessary during Ritalin LA treatment. Further clinical evaluation (e.g., rheumatology referral) may be appropriate for Ritalin LA-treated patients who develop signs or symptoms of peripheral vasculopathy.

5.7 Long-Term Suppression of Growth in Pediatric Patients

Ritalin LA is not approved for use and is not recommended in pediatric patients below 6 years of age [see Use in Specific Populations (8.4)].

CNS stimulants have been associated with weight loss and slowing of growth rate in pediatric patients.

Careful follow-up of weight and height in pediatric patients ages 7 to 10 years who were randomized to either methylphenidate or non-medication treatment groups over 14 months, as well as in naturalistic subgroups of newly

methylphenidate-treated and non-medication treated patients over 36 months (to the ages of 10 to13 years), suggests that pediatric patients who received methylphenidate for 7 days per week throughout the year had a temporary slowing in growth rate (on average, a total of about 2 cm less growth in height and 2.7 kg less growth in weight over 3 years), without evidence of growth rebound during this development period.

Closely monitor growth (weight and height) in Ritalin LA-treated pediatric patients. Pediatric patients who are not growing or gaining height or weight as expected may need to have their treatment interrupted.

5.8 Acute Angle Closure Glaucoma

There have been reports of angle closure glaucoma associated with methylphenidate treatment.

Although the mechanism is not clear, Ritalin LA-treated patients considered at risk for acute angle closure glaucoma (e.g., patients with significant hyperopia) should be evaluated by an ophthalmologist.

5.9 Increased Intraocular Pressure and Glaucoma

There have been reports of an elevation of intraocular pressure (IOP) associated with methylphenidate treatment [see Adverse Reactions (6.2)]. Prescribe Ritalin LA to patients with open-angle glaucoma or abnormally increased IOP only if the benefit of treatment is considered to outweigh the risk. Closely monitor Ritalin LA-treated patients with a history of abnormally increased IOP or open angle glaucoma.

5.10 Motor and Verbal Tics, and Worsening of Tourette’s Syndrome

CNS stimulants, including methylphenidate, have been associated with the onset or exacerbation of motor and verbal tics. Worsening of Tourette’s syndrome has also been reported [see Adverse Reactions (6.2)].

Before initiating Ritalin LA, assess the family history and clinically evaluate patients for tics or Tourette’s syndrome.

Regularly monitor Ritalin LA-treated patients for the emergence or worsening of tics or Tourette’s syndrome and

discontinue treatment if clinically appropriate.

6 ADVERSE REACTIONS

The following are discussed in more detail in other sections of the labeling:

- Abuse, Misuse, and Addiction [see Boxed Warning, Warnings and Precautions (5.1), Drug Abuse and Dependence (9.2, 9.3)]
- Known hypersensitivity to methylphenidate or other ingredients of Ritalin LA [see Contraindications (4)]
- Hypertensive crisis when used concomitantly with Monoamine Oxidase Inhibitors [see Contraindications (4), Drug Interactions (7.1)]
- Risks to Patients with Serious Cardiac Disease [see Warnings and Precautions (5.2)]
- Increased Blood Pressure and Heart Rate [see Warnings and Precautions (5.3)]
- Psychiatric Adverse Reactions [see Warnings and Precautions (5.4)]
- Priapism [see Warnings and Precautions (5.5)]
- Peripheral Vasculopathy, Including Raynaud’s Phenomenon [see Warnings and Precautions (5.6)]
- Long-Term Suppression of Growth in Pediatric Patients [see Warnings and Precautions (5.7)]
- Acute Angle Closure Glaucoma [see Warnings and Precautions (5.8)]
- Increased Intraocular Pressure and Glaucoma [see Warnings and Precautions (5.9)]
- Motor and Verbal Tics, and Worsening of Tourette’s Syndrome [see Warnings and Precautions (5.10)]

6.1 Clinical Trials Experience

Because clinical trials are conducted under widely varying conditions, adverse reaction rates observed in the clinical trials of a drug cannot be directly compared to rates in the clinical trials of another drug and may not reflect the rates observed in practice.

The clinical program for Ritalin LA consisted of 6 studies: 2 controlled clinical studies conducted in children with ADHD aged 6 to 12 years and 4 clinical pharmacology studies conducted in healthy adult volunteers. These studies included a total of 256 subjects; 195 children with ADHD and 61 healthy adult volunteers. The subjects received Ritalin LA in doses of 10 to 40 mg per day. Safety of Ritalin LA was assessed by evaluating frequency and nature of adverse events, routine laboratory tests, vital signs, and body weight. A placebo-controlled, double-blind, parallel-group study was conducted to evaluate the efficacy and safety of Ritalin LA in children with ADHD aged 6 to 12 years. All subjects received Ritalin LA for up to 4 weeks, and had their dose optimally adjusted, prior to entering the double-blind phase of the trial. In the 2-week double-blind treatment phase of this study, patients received either placebo or Ritalin LA at their individually-titrated dose (range, 10 mg to 40 mg).

Adverse reactions with an incidence greater than 5% during the initial 4-week single-blind Ritalin LA titration period of this study were headache, insomnia, upper abdominal pain, appetite decreased, and anorexia.

Adverse reactions with an incidence greater than 2% among Ritalin LA-treated subjects, during the 2-week double-blind phase of the clinical study, are shown in Table 2.

Table 2: Adverse Reactions in Greater Than 2% Ritalin LA-Treated Subjects in the 2-Week Double-Blind Phase
Preferred Term | Ritalin LA N = 65 N (%) | Placebo N = 71 N (%)
Anorexia | 2 (3.1) | 0 (0.0)
Insomnia | 2 (3.1) | 0 (0.0)

Adverse Reactions Associated with Discontinuation of Treatment

In the 2-week double-blind treatment phase of a placebo-controlled parallel-group study in children with ADHD, one Ritalin LA-treated subject (1/65, 1.5%) discontinued due to an adverse event (depressed mood).

In the single-blind titration period of this study, subjects received Ritalin LA for up to 4 weeks. During this period a total of 6 subjects (6/161, 3.7%) discontinued due to adverse events. The adverse events leading to discontinuation were anger (2 patients), hypomania, anxiety, depressed mood, fatigue, migraine, and lethargy.

6.2 Postmarketing Experience

The following adverse reactions have been identified during the post approval use of methylphenidate products. Because these reactions were reported voluntarily from a population of uncertain size, it is not always possible to estimate their frequency reliably or to establish a causal relationship to drug exposure.

Adverse Reactions Reported with Ritalin and Ritalin LA

Infections and Infestations: nasopharyngitis

Blood and the Lymphatic System Disorders: leukopenia, thrombocytopenia, anemia

Immune System Disorders: hypersensitivity reactions, including angioedema and anaphylaxis

Metabolism and Nutrition Disorders: decreased appetite, reduced weight gain, and suppression of growth during prolonged use in children

Psychiatric Disorders: insomnia, anxiety, restlessness, agitation, psychosis (sometimes with visual and tactile hallucinations), depressed mood, depression

Nervous System Disorders: headache, dizziness, tremor, dyskinesia, including choreoathetoid movements, drowsiness, convulsions, cerebrovascular disorders (including vasculitis, cerebral hemorrhages and cerebrovascular accidents), serotonin syndrome in combination with serotonergic drugs

Eye Disorders: blurred vision, difficulties in visual accommodation

Cardiac Disorders: tachycardia, palpitations, increased blood pressure, arrhythmias, angina pectoris

Respiratory, Thoracic, and Mediastinal Disorders: cough

Gastrointestinal Disorders: dry mouth, nausea, vomiting, abdominal pain, dyspepsia

Hepatobiliary Disorders: abnormal liver function, ranging from transaminase elevation to severe hepatic injury

Skin and Subcutaneous Tissue Disorders: hyperhidrosis, pruritus, urticaria, exfoliative dermatitis, scalp hair loss, erythema multiforme rash, thrombocytopenic purpura

Musculoskeletal and Connective Tissue Disorders: arthralgia, muscle cramps, rhabdomyolysis, trismus

Investigations: weight loss (adult ADHD patients)

Vascular Disorders: peripheral coldness, Raynaud's phenomenon

Adverse Reactions Reported with Other Methylphenidate-Containing Products

The list below shows adverse reactions not listed with Ritalin or Ritalin LA formulations that have been reported with other methylphenidate-containing products.

Blood and Lymphatic Disorders: pancytopenia

Immune System Disorders: hypersensitivity reactions, such as auricular swelling, bullous conditions, eruptions, exanthemas

Psychiatric Disorders: affect lability, mania, disorientation, libido changes

Nervous System Disorders: migraine, motor and verbal tics

Eye Disorders: diplopia, increased intraocular pressure, mydriasis

Cardiac Disorders: sudden cardiac death, myocardial infarction, bradycardia, extrasystole

Respiratory, Thoracic, and Mediastinal Disorders: pharyngolaryngeal pain, dyspnea

Gastrointestinal Disorders: diarrhea, constipation

Skin and Subcutaneous Tissue Disorders: angioneurotic edema, erythema, fixed drug eruption

Musculoskeletal, Connective Tissue, and Bone Disorders: myalgia, muscle twitching

Renal and Urinary Disorders: hematuria

Reproductive System and Breast Disorders: gynecomastia

General Disorders: fatigue, hyperpyrexia

Urogenital Disorders: priapism

7 DRUG INTERACTIONS

7.1 Clinically Important Drug Interactions with Ritalin LA

Table 3 presents clinically important drug interactions with Ritalin LA.

Table 3: Clinically Important Drug Interactions with Ritalin LA
Monoamine Oxidase Inhibitors (MAOI)
Clinical impact | Concomitant use of MAOIs and CNS stimulants, including Ritalin LA, can cause hypertensive crisis. Potential outcomes include death, stroke, myocardial infarction, aortic dissection, ophthalmological complications, eclampsia, pulmonary edema, and renal failure [see Contraindications (4)].
Intervention | Concomitant use of Ritalin LA with MAOIs or within 14 days after discontinuing MAOI treatment is contraindicated.
Antihypertensive Drugs
Clinical impact | Ritalin LA may decrease the effectiveness of drugs used to treat hypertension [see Warnings and Precautions (5.3)].
Intervention | Monitor blood pressure and adjust the dosage of the antihypertensive drug as needed.
Halogenated Anesthetics
Clinical impact | Concomitant use of halogenated anesthetics and Ritalin LA may increase the risk of sudden blood pressure and heart rate increase during surgery.
Intervention | Avoid use of Ritalin LA in patients being treated with anesthetics on the day of surgery.
Risperidone
Clinical impact | Combined use of methylphenidate with risperidone when there is a change, whether an increase or decrease, in dosage of either or both medications, may increase the risk of extrapyramidal symptoms (EPS)
Intervention | Monitor for signs of EPS

8 USE IN SPECIFIC POPULATIONS

8.1 Pregnancy

Pregnancy Exposure Registry

There is a pregnancy exposure registry that monitors pregnancy outcomes in women exposed to ADHD medications, including Ritalin LA during pregnancy. Healthcare providers are encouraged to register patients by calling the National Pregnancy Registry for ADHD medications at 1-866-961-2388 or visiting https://womensmentalhealth.org/adhd-medications/.

Risk Summary

Published studies and postmarketing reports on methylphenidate use during pregnancy have not identified a drug-associated risk of major birth defects, miscarriage or adverse maternal or fetal outcomes. There may be risks to the fetus associated with the use of CNS stimulants use during pregnancy (see Clinical Considerations).

No effects on morphological development were observed in embryo-fetal development studies with oral administration of methylphenidate to pregnant rats and rabbits during organogenesis at doses up to 10 and 15 times, respectively, the maximum recommended human dose (MRHD) of 60 mg/day given to adolescents on a mg/m^2 basis. However, spina bifida was observed in rabbits at a dose 52 times the MRHD given to adolescents. A decrease in pup body weight was observed in a pre- and post-natal development study with oral administration of methylphenidate to rats throughout pregnancy and lactation at doses 6 times the MRHD given to adolescents (see Data).

The estimated background risk of major birth defects and miscarriage for the indicated population is unknown. All pregnancies have a background risk of birth defect, loss, or other adverse outcomes. In the U.S. general population, the estimated background risk of major birth defects and miscarriage in clinically recognized pregnancies is 2% to 4% and 15% to 20%, respectively.

Clinical Considerations

Fetal/Neonatal Adverse Reactions

CNS stimulants, such as Ritalin LA, can cause vasoconstriction and thereby decrease placental perfusion. No fetal and/or neonatal adverse reactions have been reported with the use of therapeutic doses of methylphenidate during pregnancy; however, premature delivery and low birth-weight-infants have been reported in amphetamine-dependent mothers.

Data

Animal Data

In embryo-fetal development studies conducted in rats and rabbits, methylphenidate was administered orally at doses of up to 75 and 200 mg/kg/day, respectively, during the period of organogenesis. Malformations (increased incidence of fetal spina bifida) were observed in rabbits at the highest dose, which is approximately 52 times the MRHD of 60 mg/day given to adolescents on a mg/m^2 basis. The no effect level for embryo-fetal development in rabbits was 60 mg/kg/day (15 times the MRHD given to adolescents on a mg/m^2 basis). There was no evidence of morphological development effects in rats, although increased incidences of fetal skeletal variations were seen at the highest dose level (10 times the MRHD of 60 mg/day given to adolescents on a mg/m^2 basis), which was also maternally toxic. The no effect level for embryo-fetal development in rats was 25 mg/kg/day (3 times the MRHD on a mg/m^2 basis). When methylphenidate was administered to rats throughout pregnancy and lactation at doses of up to 45 mg/kg/day, offspring body weight gain was decreased at the highest dose (6 times the MRHD of 60 mg/day given to adolescents on a mg/m^2 basis), but no other effects on postnatal development were observed. The no effect level for pre- and post-natal development in rats was 15 mg/kg/day (approximately 2 times the MRHD given to adolescents on a mg/m^2 basis).

8.2 Lactation

Risk Summary

Limited published literature, based on milk sampling from seven mothers reports that methylphenidate is present in human milk, which resulted in infant doses of 0.16% to 0.7% of the maternal weight-adjusted dosage and a milk/plasma ratio ranging between 1.1 and 2.7. There are no reports of adverse effects on the breastfed infant and no effects on milk production. Long-term neurodevelopmental effects on infants from stimulant exposure are unknown. The developmental and health benefits of breastfeeding should be considered along with the mother’s clinical need for Ritalin LA and any potential adverse effects on the breastfed infant from Ritalin LA or from the underlying maternal condition.

Clinical Considerations

Monitor breastfeeding infants for adverse reactions, such as agitation, insomnia, anorexia, and reduced weight gain.

8.4 Pediatric Use

The safety and effectiveness of Ritalin LA have not been established in pediatric patients below the age of 6 years.

In studies evaluating extended-release methylphenidate products, patients 4 to <6 years of age had higher systemic methylphenidate exposures than those observed in older pediatric patients at the same dosage. Pediatric patients 4 to <6 years of age also had a higher incidence of adverse reactions, including weight loss.

The safety and effectiveness of Ritalin LA for the treatment of ADHD have been established in pediatric patients aged 6 to 12 years.

Long-Term Suppression of Growth

Growth should be monitored during treatment with stimulants, including Ritalin LA. Pediatric patients who are not growing or gaining weight as expected may need to have their treatment interrupted [see Warnings and Precautions (5.7)].

Juvenile Animal Toxicity Data

Rats treated with methylphenidate early in the postnatal period through sexual maturation demonstrated a decrease in spontaneous locomotor activity in adulthood. A deficit in acquisition of a specific learning task was observed in females only. The doses at which these findings were observed are at least 4 times the MRHD of 60 mg/day given to children on a mg/m^2 basis.

In a study conducted in young rats, methylphenidate was administered orally at doses of up to 100 mg/kg/day for 9 weeks, starting early in the postnatal period (postnatal Day 7) and continuing through sexual maturity (postnatal Week 10). When these animals were tested as adults (postnatal Weeks 13 to 14), decreased spontaneous locomotor activity was observed in males and females previously treated with 50 mg/kg/day (approximately 4 times the MRHD of 60 mg/day given to children on a mg/m^2 basis) or greater, and a deficit in the acquisition of a specific learning task was seen in females exposed to the highest dose (8 times the MRHD given to children on a mg/m^2 basis). The no effect level for juvenile neurobehavioral development in rats was 5 mg/kg/day (approximately 0.5 times the MRHD given to children on a mg/m^2 basis). The clinical significance of the long-term behavioral effects observed in rats is unknown.

8.5 Geriatric Use

Ritalin LA has not been studied in the geriatric population.

9 DRUG ABUSE AND DEPENDENCE

9.1 Controlled Substance

Ritalin LA contains methylphenidate hydrochloride, a Schedule II controlled substance.

9.2 Abuse

Ritalin LA has a high potential for abuse and misuse which can lead to the development of a substance use disorder,

including addiction [see Warnings and Precautions (5.1)]. Ritalin LA can be diverted for non-medical use into illicit channels or distribution.

Abuse is the intentional non-therapeutic use of a drug, even once, to achieve a desired psychological or physiological effect. Misuse is the intentional use, for therapeutic purposes, of a drug by an individual in a way other than prescribed by a health care provider or for whom it was not prescribed. Drug addiction is a cluster of behavioral, cognitive, and physiological phenomena that may include a strong desire to take the drug, difficulties in controlling drug use (e.g., continuing drug use despite harmful consequences, giving a higher priority to drug use than other activities and obligations), and possible tolerance or physical dependence.

Misuse and abuse of methylphenidate hydrochloride may cause increased heart rate, respiratory rate, or blood pressure; sweating; dilated pupils; hyperactivity; restlessness; insomnia; decreased appetite; loss of coordination; tremors; flushed skin; vomiting; and/or abdominal pain. Anxiety, psychosis, hostility, aggression, and suicidal or homicidal ideation have also been observed with CNS stimulants abuse and/or misuse. Misuse and abuse of CNS stimulants, including Ritalin LA, can result in overdose and death [see Overdosage (10)], and this risk is increased with higher doses or unapproved methods of administration, such as snorting or injection.

9.3 Dependence

Physical Dependence

Ritalin LA may produce physical dependence. Physical dependence is a state that develops as a result of physiological adaptation in response to repeated drug use, manifested by withdrawal signs and symptoms after abrupt discontinuation or

a significant dose reduction of a drug.

Withdrawal signs and symptoms after abrupt discontinuation or dose reduction following prolonged use of CNS stimulants including Ritalin LA include dysphoric mood; depression; fatigue; vivid, unpleasant dreams; insomnia or

hypersomnia; increased appetite; and psychomotor retardation or agitation.

Tolerance

Ritalin LA may produce tolerance. Tolerance is a physiological state characterized by a reduced response to a drug after

repeated administration (i.e., a higher dose of a drug is required to produce the same effect that was once obtained at a

lower dose).

10 OVERDOSAGE

Clinical Effects of Overdose

Overdose of CNS stimulants is characterized by the following sympathomimetic effects:

- Cardiovascular effects including tachyarrhythmias, and hypertension or hypotension. Vasospasm, myocardial

infarction, or aortic dissection may precipitate sudden cardiac death. Takotsubo cardiomyopathy may develop.

- CNS effects including psychomotor agitation, confusion, and hallucinations. Serotonin syndrome, seizures,

cerebral vascular accidents, and coma may occur.

- Life-threatening hyperthermia (temperatures greater than 104°F) and rhabdomyolysis may develop.

Overdose Management

Consider the possibility of multiple drug ingestion. The pharmacokinetic profile of Ritalin LA should be considered when treating patients with overdose. Because methylphenidate has a large volume of distribution and is rapidly metabolized,

dialysis is not useful. Consider contacting the Poison Help line (1-800-222-1222) or a medical toxicologist for additional overdose management recommendations.

11 DESCRIPTION

Ritalin LA contains methylphenidate hydrochloride, a CNS stimulant.

Ritalin LA extended-release capsules is an extended-release formulation of methylphenidate for oral administration with a bi-modal release profile. Each bead-filled Ritalin LA capsule contains half the dose as immediate-release beads and half as enteric-coated beads, thus providing an immediate release of methylphenidate and a second delayed release of methylphenidate.

The active substance in Ritalin LA is methyl α-phenyl-2-piperidineacetate hydrochloride, and its structural formula is

Methylphenidate hydrochloride USP is a white, odorless, fine crystalline powder. Its solutions are acid to litmus. It is freely soluble in water and in methanol, soluble in alcohol, and slightly soluble in chloroform and in acetone. Its molecular weight is 269.77 g/mol.

Inactive ingredients: ammonio methacrylate copolymer, black iron oxide (10 and 40 mg capsules only), gelatin, methacrylic acid copolymer, polyethylene glycol, red iron oxide (10 and 40 mg capsules only), sugar spheres, talc, titanium dioxide, triethyl citrate, and yellow iron oxide (10, 30, and 40 mg capsules only).

12 CLINICAL PHARMACOLOGY

12.1 Mechanism of Action

Methylphenidate hydrochloride is a CNS stimulant. The mode of therapeutic action in ADHD is not known.

12.2 Pharmacodynamics

Methylphenidate is a racemic mixture comprised of the d- and l-threo enantiomers. The d-threo enantiomer is more pharmacologically active than the l-threo enantiomer. Methylphenidate blocks the reuptake of norepinephrine and dopamine into the presynaptic neuron and increases the release of these monoamines into the extraneuronal space.

Cardiac Electrophysiology

A formal QT study has not been conducted in patients taking Ritalin LA.

The effect of dexmethylphenidate, the pharmacologically active d-enantiomer of Ritalin, on the QT interval was evaluated in a double-blind, placebo- and open-label active (moxifloxacin)-controlled study following single doses of dexmethylphenidate XR 40 mg (maximum recommended adult total daily dosage) in 75 healthy volunteers. Electrocardiograms were collected up to 12 hours postdose. Frederica’s method for heart rate correction was employed to derive the corrected QT interval (QTcF). The maximum mean prolongation of QTcF intervals was less than 5 ms, and the upper limit of the 90% confidence interval was below 10 ms for all time matched comparisons versus placebo. This was below the threshold of clinical concern and there was no evident-exposure response relationship.

12.3 Pharmacokinetics

Ritalin LA produces a bi-modal plasma concentration-time profile (i.e., 2 distinct peaks approximately 4 hours apart) when administered orally to children diagnosed with ADHD and healthy adults.

No accumulation of methylphenidate is expected following multiple once daily oral dosing with Ritalin LA, however, there is a slight upward trend in the methylphenidate area under the curve and peak plasma concentrations (Cmax1 and Cmax2) after oral administration of Ritalin LA 20 mg and 40 mg capsules to adults.

Absorption

The absolute oral bioavailability of methylphenidate in children was 22% ± 8% for d-methylphenidate and 5% ± 3% for l-methylphenidate. The relative bioavailability of Ritalin LA given once daily is comparable to the same total dose of Ritalin tablets given in 2 doses 4 hours apart in both children and adults.

The initial rate of absorption for Ritalin LA is similar to that of Ritalin tablets as shown by the similar rate parameters between the 2 formulations, i.e., initial lag time (Tlag), first peak concentration (Cmax1), and time to the first peak (Tmax1), which is reached in 1 to 3 hours. The mean time to the interpeak minimum (Tminip), and time to the second peak (Tmax2) are also similar for Ritalin LA given once daily and Ritalin tablets given in 2 doses 4 hours apart (see Figure 1 and Table 1), although the ranges observed are greater for Ritalin LA.

Ritalin LA given once daily exhibits a lower second peak concentration (Cmax2), higher interpeak minimum concentrations (Cminip), and less peak and trough fluctuations than Ritalin tablets given in 2 doses given 4 hours apart. This is due to an earlier onset and more prolonged absorption from the delayed-release beads (see Figure 1 and Table 4).

Figure 1: Mean Plasma Concentration Time-profile of Methylphenidate After a Single Dose of Ritalin LA 40 mg and Ritalin 20 mg Given in Two Doses 4 Hours Apart

Table 4: Mean ± SD and Range of Pharmacokinetic Parameters of Methylphenidate After a Single Dose of Ritalin LA and Ritalin Given in Two Doses 4 Hours Apart
Population | Children |  | Adult Males
Formulation Dose | Ritalin 10 mg & 10 mg | Ritalin LA 20 mg | Ritalin 10 mg & 10 mg | Ritalin LA 20 mg
N | 21 | 18 | 9 | 8
Tlag (h) | 0.24 ± 0.44 | 0.28 ± 0.46 | 1.0 ± 0.5 | 0.7 ± 0.2
Tlag (h) | 0 - 1 | 0 - 1 | 0.7 - 1.3 | 0.3 - 1.0
Tmax1 (h) | 1.8 ± 0.6 | 2.0 ± 0.8 | 1.9 ± 0.4 | 2.0 ± 0.9
Tmax1 (h) | 1 - 3 | 1 - 3 | 1.3 - 2.7 | 1.3 - 4.0
Cmax1 (ng/mL) | 10.2 ± 4.2 | 10.3 ± 5.1 | 4.3 ± 2.3 | 5.3 ± 0.9
Cmax1 (ng/mL) | 4.2 - 20.2 | 5.5 - 26.6 | 1.8 - 7.5 | 3.8 - 6.9
Tminip (h) | 4.0 ± 0.2 | 4.5 ± 1.2 | 3.8 ± 0.4 | 3.6 ± 0.6
Tminip (h) | 4 - 5 | 2 - 6 | 3.3 - 4.3 | 2.7 - 4.3
Cminip (ng/mL) | 5.8 ± 2.7 | 6.1 ± 4.1 | 1.2 ± 1.4 | 3.0 ± 0.8
Cminip (ng/mL) | 3.1 - 14.4 | 2.9 - 21.0 | 0.0 - 3.7 | 1.7 - 4.0
Tmax2 (h) | 5.6 ± 0.7 | 6.6 ± 1.5 | 5.9 ± 0.5 | 5.5 ± 0.8
Tmax2 (h) | 5 - 8 | 5 - 11 | 5.0 - 6.5 | 4.3 - 6.5
Cmax2 (ng/mL) | 15.3 ± 7.0 | 10.2 ± 5.9 | 5.3 ± 1.4 | 6.2 ± 1.6
Cmax2 (ng/mL) | 6.2 - 32.8 | 4.5 - 31.1 | 3.6 - 7.2 | 3.9 - 8.3
AUC(0-∞) (ng/mL x h-1) | 102.4 ± 54.6 | 86.6 ± 64.0a | 37.8 ± 21.9 | 45.8 ± 10.0
AUC(0-∞) (ng/mL x h-1) | 40.5 - 261.6 | 43.3 - 301.44 | 14.3 - 85.3 | 34.0 - 61.6
t1/2 (h) | 2.5 ± 0.8 | 2.4 ± 0.7a | 3.5 ± 1.9 | 3.3 ± 0.4
t1/2 (h) | 1.8 - 5.3 | 1.5 - 4.0 | 1.3 - 7.7 | 3.0 - 4.2
aN = 15.

Effect of Food

Administration times relative to meals and meal composition may need to be individually titrated.

When Ritalin LA was administered with a high fat breakfast to adults, Ritalin LA had a longer lag time until absorption began and variable delays in the time until the first peak concentration, the time until the interpeak minimum, and the time until the second peak. The first peak concentration and the extent of absorption were unchanged after food relative to the fasting state, although the second peak was approximately 25% lower. The effect of a high fat lunch was not examined.

There were no differences in the pharmacokinetics of Ritalin LA when administered with applesauce, compared to administration in the fasting condition. There is no evidence of dose dumping in the presence or absence of food.

Effect of Alcohol

An in vitro study was conducted to explore the effect of alcohol on the release characteristics of methylphenidate from the Ritalin LA 40 mg capsule dosage form. At an alcohol concentration of 40% there was a 98% release of methylphenidate in the first hour. The results with the 40 mg capsule are considered to be representative of the other available capsule strengths.

Distribution

Binding to plasma proteins is low (10% to 33%). The volume of distribution was 2.65 ± 1.11 L/kg for d-methylphenidate and 1.80 ± 0.91 L/kg for l-methylphenidate.

Elimination

The systemic clearance is 0.40 ± 0.12 L/h/kg for d-methylphenidate and 0.73 ± 0.28 L/h/kg for l-methylphenidate. In studies with Ritalin LA and Ritalin tablets in adults, methylphenidate from Ritalin tablets is eliminated from plasma with an average half-life of about 3.5 hours, (range, 1.3 to 7.7 hours). In children the average half-life is about 2.5 hours, with a range of about 1.5 to 5.0 hours. The rapid half-life in both children and adults may result in un-measurable concentrations between the morning and mid-day doses with Ritalin tablets. No accumulation of methylphenidate is expected following multiple once a day oral dosing with Ritalin LA. The half-life of ritalinic acid is about 3 to 4 hours.

Metabolism

The absolute oral bioavailability of methylphenidate in children was 22% ± 8% for d-methylphenidate and 5% ± 3% for l-methylphenidate, suggesting pronounced presystemic metabolism. Biotransformation of methylphenidate by the carboxylesterase CES1A1 is rapid and extensive leading to the main, de-esterified metabolite α-phenyl-2-piperidine acetic acid (ritalinic acid), which has little or no pharmacologic activity. Only small amounts of hydroxylated metabolites (e.g., hydroxymethylphenidate and hydroxyritalinic acid) are detectable in plasma. Therapeutic activity is principally due to the parent compound.

Excretion

After oral administration of an immediate release formulation of methylphenidate, 78% to 97% of the dose is excreted in the urine and 1% to 3% in the feces in the form of metabolites within 48 to 96 hours. Only small quantities (less than 1%) of unchanged methylphenidate appear in the urine. Most of the dose is excreted in the urine as ritalinic acid (60% to 86%), the remainder being accounted for by minor metabolite.

Studies in Specific Populations

Male and Female Patients

There were no apparent gender differences in the pharmacokinetics of methylphenidate between healthy male and female adults when administered Ritalin LA.

Racial or Ethnic Groups

There is insufficient experience with the use of Ritalin LA to detect ethnic variations in pharmacokinetics.

Pediatric Patients

The pharmacokinetics of Ritalin LA was examined in 18 children with ADHD between 7 and 12 years of age. Fifteen of these children were between 10 and 12 years of age. The time until the between peak minimum, and the time until the second peak were delayed and more variable in children compared to adults. After a 20-mg dose of Ritalin LA, concentrations in children were approximately twice the concentrations observed in 18- to 35- year- old adults. This higher exposure is almost completely due to the smaller body size and total volume of distribution in children, as apparent clearance normalized to body weight is independent of age.

Patients with Renal Impairment

Ritalin LA has not been studied in renally-impaired patients. Renal impairment is expected to have minimal effect on the pharmacokinetics of methylphenidate since less than 1% of a radiolabeled dose is excreted in the urine as unchanged compound, and the major metabolite (ritalinic acid), has little or no pharmacologic activity.

Patients with Hepatic Impairment

Ritalin LA has not been studied in patients with hepatic impairment. Hepatic impairment is expected to have minimal effect on the pharmacokinetics of methylphenidate since it is metabolized primarily to ritalinic acid by nonmicrosomal hydrolytic esterases that are widely distributed throughout the body.

13 NONCLINICAL TOXICOLOGY

13.1 Carcinogenesis, Mutagenesis, and Impairment of Fertility

Carcinogenesis

In a lifetime carcinogenicity study carried out in B6C3F1 mice, methylphenidate caused an increase in hepatocellular adenomas, and in males only, an increase in hepatoblastomas at a daily dose of approximately 60 mg/kg/day. This dose is approximately 2 times the MRHD of 60 mg/day given to children on a mg/m2 basis. Hepatoblastoma is a relatively rare rodent malignant tumor type. There was no increase in total malignant hepatic tumors. The mouse strain used is sensitive to the development of hepatic tumors, and the significance of these results to humans is unknown.

Methylphenidate did not cause any increase in tumors in a lifetime carcinogenicity study carried out in F344 rats; the highest dose used was approximately 45 mg/kg/day, which is approximately 4 times the MRHD (children) on a mg/m2 basis.

In a 24-week carcinogenicity study in the transgenic mouse strain p53+/-, which is sensitive to genotoxic carcinogens, there was no evidence of carcinogenicity. Male and female mice were fed diets containing the same concentration of methylphenidate as in the lifetime carcinogenicity study; the high-dose groups were exposed to 60 to 74 mg/kg/day of methylphenidate.

Mutagenesis

Methylphenidate was not mutagenic in the in vitro Ames reverse mutation assay, in the in vitro mouse lymphoma cell forward mutation assay, or in the in vitro chromosomal aberration assay using human lymphocytes. Sister chromatid exchanges and chromosome aberrations were increased, indicative of a weak clastogenic response, in an in vitro assay in cultured Chinese Hamster Ovary cells. Methylphenidate was negative in vivo in males and females in the mouse bone marrow micronucleus assay.

Impairment of Fertility

Methylphenidate did not impair fertility in male or female mice that were fed diets containing the drug in an 18-week continuous breeding study. The study was conducted at doses up to 160 mg/kg/day, approximately 10 times the maximum recommended dose of 60 mg/day given to adolescents on a mg/m^2 basis.

14 CLINICAL STUDIES

14.1 Children and Adolescents

Ritalin LA was evaluated in a randomized, double-blind, placebo-controlled, parallel group clinical study in which 134 children, ages 6 to 12 years, with DSM-IV diagnoses of ADHD received a single morning dose of Ritalin LA in the range of 10 to 40 mg/day, or placebo, for up to 2 weeks. The doses used were the optimal doses established in a previous individual dose titration phase. In that titration phase, 53 of 164 patients (32%) started on a daily dose of 10 mg and 111 of 164 patients (68%) started on a daily dose of 20 mg or higher. The patient’s regular schoolteacher completed the Conners ADHD/DSM-IV Scale for Teachers (CADS-T) at baseline and the end of each week. The CADS-T assesses symptoms of hyperactivity and inattention. The change from baseline of the (CADS-T) scores during the last week of treatment was analyzed as the primary efficacy parameter. Patients treated with Ritalin LA showed a statistically significant improvement in symptom scores from baseline [Mean (final score - baseline) = -10.7 points] over patients who received placebo [Mean (final score - baseline) = +2.8 points]. The lower the final score on the CADS-T scale from baseline, the less severe the disease is. This demonstrates that a single morning dose of Ritalin LA exerts a treatment effect in ADHD.

Figure 2: CADS-T Total Subscale - Mean Change from Baseline*

16 HOW SUPPLIED/STORAGE AND HANDLING

- 10 mg extended-release capsules (NDC 0078-0424-05) white/light brown, (imprinted “NVR R10”) supplied in bottles of 100
- 20 mg extended-release capsules (NDC 0078-0370-05) white, (imprinted “NVR R20”) supplied in bottles of 100
- 30 mg extended-release capsules (NDC 0078-0371-05) yellow, (imprinted “NVR R30”) supplied in bottles of 100
- 40 mg extended-release capsules (NDC 0078-0372-05) light brown, (imprinted “NVR R40”) supplied in bottles of 100

Store at 20°C to 25°C (68°F to 77°F); excursions permitted between 15°C and 30°C (59°F and 86°F) [See USP controlled room temperature].

Dispense in tight container (USP).

17 PATIENT COUNSELING INFORMATION

Advise the patient to read the FDA-approved patient labeling (Medication Guide).

Abuse, Misuse, and Addiction

Educate patients and their families about the risks of abuse, misuse, and addiction of Ritalin LA, which can lead to

overdose and death, and proper disposal of any unused drug [see Warnings and Precautions (5.1), Drug Abuse and

Dependence (9.2), Overdosage (10)]. Advise patients to store Ritalin LA in a safe place, preferably locked, and instruct patients to not give Ritalin LA to anyone else.

Risks to Patients with Serious Cardiac Disease

Advise patients that there are potential risks to patients with serious cardiac disease, including sudden death, with

Ritalin LA use. Instruct patients to contact a healthcare provider immediately if they develop symptoms, such as

exertional chest pain, unexplained syncope, or other symptoms suggestive of cardiac disease [see Warnings and

Precautions (5.2)].

Increased Blood Pressure and Heart Rate

Instruct patients that Ritalin LA can cause elevations of their blood pressure and pulse rate [see Warnings and Precautions (5.3)].

Psychiatric Adverse Reactions

Advise patients that Ritalin LA, at recommended doses, can cause psychotic or manic symptoms, even in patients without prior history of psychotic symptoms or mania [see Warnings and Precautions (5.4)].

Priapism

Advise patients of the possibility of painful or prolonged penile erections (priapism). Instruct them to seek immediate medical attention in the event of priapism [see Warnings and Precautions (5.5)].

Circulation Problems in Fingers and Toes [Peripheral Vasculopathy, Including Raynaud’s Phenomenon]

Instruct patients beginning treatment with Ritalin LA about the risk of peripheral vasculopathy, including Raynaud’s phenomenon, and associated signs and symptoms: fingers or toes may feel numb, cool, painful, and/or may change color from pale, to blue, to red. Instruct patients to report to their physician any new numbness, pain, skin color change, or sensitivity to temperature in fingers or toes.

Instruct patients to call their physician immediately with any signs of unexplained wounds appearing on fingers or toes while taking Ritalin LA. Further clinical evaluation (e.g., rheumatology referral) may be appropriate for certain patients [see Warnings and Precautions (5.6)].

Long Term Suppression of Growth in Pediatric Patients

Advise patients that Ritalin LA may cause slowing of growth and weight loss [see Warnings and Precautions (5.7)].

Increased Intraocular Pressure (IOP) and Glaucoma

Advise patients that IOP and glaucoma may occur during treatment with Ritalin LA [see Warnings and Precautions (5.9)].

Motor and Verbal Tics and Worsening of Tourette’s Syndrome

Advise patients that motor and verbal tics and worsening of Tourette’s Syndrome may occur during treatment with

Ritalin LA. Instruct patients to notify their healthcare provider if emergence of new tics or worsening of tics or Tourette’s syndrome occurs [see Warnings and Precautions (5.10)].

Alcohol Effect

Advise patients to avoid alcohol while taking Ritalin LA. Consumption of alcohol while taking Ritalin LA may result in a more rapid release of the dose of methylphenidate [see Clinical Pharmacology (12.3)].

Pregnancy Registry

Advise patients that there is a pregnancy exposure registry that monitors pregnancy outcomes in patients exposed to Ritalin LA during pregnancy [see Use in Specific Populations (8.1)].

Distributed by:
Novartis Pharmaceuticals Corporation
East Hanover, New Jersey 07936

MEDICATION GUIDE
RITALIN LA® (rit-ah-lin LA)
(methylphenidate hydrochloride)
extended-release capsules for oral use, CII

What is the most important information I should know about RITALIN LA?

RITALIN LA may cause serious side effects, including:

- Abuse, misuse, and addiction. RITALIN LA has a high chance for abuse and misuse and may lead to substance use problems, including addiction. Misuse and abuse of RITALIN LA, other methylphenidate containing medicines, and amphetamine containing medicines, can lead to overdose and death. The risk of overdose and death is increased with higher doses of RITALIN LA or when it is used in ways that are not approved, such as snorting or injection.

o Your healthcare provider should check you or your child’s risk for abuse, misuse, and addiction before starting

treatment with RITALIN LA and will monitor you or your child during treatment.

o RITALIN LA may lead to physical dependence after prolonged use, even if taken as directed by your healthcare provider.

o Do not give RITALIN LA to anyone else. See “What is RITALIN LA?” for more information.

o Keep RITALIN LA in a safe place and properly dispose of any unused medicine. See “How should I store RITALIN LA?” for more information.

o Tell your healthcare provider if you or your child have ever abused or been dependent on alcohol, prescription

medicines, or street drugs.

- Risks for people with serious heart disease. Sudden death has happened in people who have heart defects or other serious heart disease.

Your healthcare provider should check you or your child carefully for heart problems before starting RITALIN LA.

Tell your healthcare provider if you or your child have any heart problems, heart disease, or heart defects.

Call your healthcare provider or go to the nearest hospital emergency room right away if you or your child has any signs of heart problems, such as chest pain, shortness of breath, or fainting while taking RITALIN LA.

- Increased blood pressure and heart rate.

Your healthcare provider should check you or your child’s blood pressure and heart rate regularly during treatment with RITALIN LA.

- Mental (psychiatric) problems:

All Patients

o new or worse behavior and thought problems

o new or worse bipolar illness

o new psychotic symptoms (such as hearing voices, believing things that are not true, are suspicious) or new manic

symptoms

Tell your healthcare provider about any mental problems you or your child have, or about a family history of suicide,

bipolar illness, or depression.

Call your healthcare provider right away if you or your child have any new or worsening mental symptoms or problems while taking RITALIN LA, especially seeing or hearing things that are not real, believing things that are not real, or are suspicious.

What is RITALIN LA?

RITALIN LA is a central nervous system (CNS) stimulant prescription medicine. It is used for the treatment of

Attention Deficit Hyperactivity Disorder (ADHD). RITALIN LA may help increase attention and decrease impulsiveness and hyperactivity in patients with ADHD.

RITALIN LA should be used as a part of a total treatment program for ADHD that may include counseling or other therapies.

Ritalin LA is not recommended for use in children under 6 years of age with ADHD.

RITALIN LA is a federally controlled substance (CII) because it contains methylphenidate that can be a target for people who abuse prescription medicines or street drugs. Keep RITALIN LA in a safe place to protect it from theft. Never give your RITALIN LA to anyone else because it may cause death or harm them. Selling or giving away RITALIN LA may harm others and is against the law.

Who should not take RITALIN LA?

RITALIN LA should not be taken if you or your child:

- are allergic to methylphenidate hydrochloride, or any of the ingredients in RITALIN LA. See the end of this Medication Guide for a complete list of ingredients in RITALIN LA.
- are taking or have taken within the past 14 days an anti-depression medicine called a monoamine oxidase inhibitor (MAOI).

RITALIN LA may not be right for you or your child. Before starting RITALIN LA, tell your or your child’s healthcare provider about all health conditions (or a family history of), including:

- heart problems, heart disease, heart defects, or high blood pressure
- mental problems, including psychosis, mania, bipolar illness, or depression
- circulation problems in fingers or toes
- have eye problems, including increased pressure in your eye, glaucoma, or problems with your close-up vision (farsightedness)
- have or had repeated movements or sounds (tics) or Tourette’s syndrome, or have a family history of tics or Tourette’s syndrome.
- if you are pregnant or plan to become pregnant. It is not known if RITALIN LA will harm your unborn baby.
- There is a pregnancy registry for females who are exposed to ADHD medications, including RITALIN LA during
pregnancy. The purpose of the registry is to collect information about the health of females exposed to RITALIN LA and their baby. If you or your child becomes pregnant during treatment with RITALIN LA, talk to your healthcare provider about registering with the National Pregnancy Registry of ADHD medications at 1-866-961-2388 or visit online at https://womensmentalhealth.org/adhd- medications/.
- if you are breastfeeding or plan to breastfeed. RITALIN LA passes into your breast milk. Talk to your healthcare provider about the best way to feed the baby during treatment with RITALIN LA.

Tell your healthcare provider about all of the medicines that you or your child take, including prescription and over-the-counter medicines, vitamins, and herbal supplements. RITALIN LA and some medicines may interact with each other and cause serious side effects. Sometimes the doses of other medicines will need to be adjusted while taking RITALIN LA.

Your healthcare provider will decide whether RITALIN LA can be taken with other medicines.

Especially tell your healthcare provider if you or your child takes:

- anti-depression medicines, including MAOIs
- blood pressure medicines (anti-hypertensive)
- risperidone

Know the medicines that you or your child takes. Keep a list of your medicines with you to show your healthcare provider and pharmacist.

- You should not take RITALIN LA on the day of your operation if a certain type of anesthetic is used. This is because there is a chance of a sudden rise in blood pressure and heart rate during the operation.

Do not start any new medicine while taking RITALIN LA without talking to your healthcare provider first.

How should RITALIN LA be taken?

- Take RITALIN LA exactly as prescribed. Your healthcare provider may adjust the dose until it is right for you or your child.
Take RITALIN LA once a day in the morning. RITALIN LA is an extended-release capsule.
- Do not chew or crush RITALIN LA capsules or the medicine inside the capsule. Swallow RITALIN LA capsules whole with water or other liquids.
- If you cannot swallow the capsule whole, open it and sprinkle the medicine over a spoonful of applesauce. Swallow the applesauce and medicine mixture without chewing. Follow with a drink of water or other liquid.
- You should avoid drinking alcohol during treatment with RITALIN LA. This may cause a faster release of RITALIN LA.

Your healthcare provider may do regular checks of the blood, heart, and blood pressure while taking RITALIN LA.

Children should have their height and weight checked often while taking RITALIN LA. If you or your child take too much RITALIN LA, call your healthcare provider or Poison Help line at 1-800-222-1222 or go to the nearest hospital emergency room right away.

What are possible side effects of RITALIN LA?

- see “What is the most important information I should know about RITALIN LA?” for information on reported heart and mental problems.
- painful and prolonged erections (priapism) have occurred with methylphenidate. If you or your child develops priapism, seek medical help right away. Because of the potential for lasting damage, priapism should be evaluated by a healthcare provider immediately.
- circulation problems in fingers and toes (peripheral vasculopathy, including Raynaud’s phenomenon):
  - fingers or toes may feel numb, cool, painful
  - fingers or toes may change color from pale, to blue, to red

Tell your healthcare provider if you or your child have numbness, pain, skin color change, or sensitivity to temperature in the fingers or toes.

Call your healthcare provider right away if you have or your child has any signs of unexplained wounds appearing on fingers or toes while taking RITALIN LA.

- Slowing of growth (height and weight) in children. Children should have their height and weight checked often during treatment with RITALIN LA. RITALIN LA treatment may be stopped if your child is not growing or gaining weight.
- Eye problems (increased pressure in the eye and glaucoma). Call your healthcare provider right away if you or your child develop changes in your vision or eye pain, swelling, or redness.
- New or worsening tics or worsening Tourette’s syndrome. Tell your healthcare provider if you or your child get any new or worsening tics or worsening Tourette’s syndrome during treatment with RITALIN LA.
- Common side effects include:
  - fast heartbeat
  - abnormal heartbeat (palpitations)
  - trouble sleeping
  - nervousness
  - sweating a lot
  - decreased appetite
  - nausea
  - stomach pain

Call your doctor for medical advice about side effects. You may report side effects to FDA at 1-800-FDA-1088.

How should I store RITALIN LA?

- Store RITALIN LA in a safe place and in a tightly closed container at room temperature, 68°F to 77°F (20°C to 25°C).
- Protect from moisture.
- Dispose of remaining, unused, or expired RITALIN LA by a medicine take-back program at a U.S. Drug Enforcement Administration (DEA) authorized collection site. If no take-back program or DEA authorized collector is available, mix RITALIN LA with an undesirable, nontoxic substance, such as dirt, cat litter, or used coffee grounds to make it less appealing to children and pets. Place the mixture in a container, such as a sealed plastic bag and throw away RITALIN LA in the household trash. Visit www.fda.gov/drugdisposal for additional information on disposal of unused medicines.
- Keep RITALIN LA and all medicines out of the reach of children.

General information about the safe and effective use of RITALIN LA.

Medicines are sometimes prescribed for purposes other than those listed in a Medication Guide. You can ask your pharmacist or healthcare provider for information about RITALIN LA that is written for healthcare professionals. Do not use RITALIN LA for a condition for which it was not prescribed. Do not give RITALIN LA to other people, even if they have the same symptoms. It may harm them and it is against the law.

What are the ingredients in RITALIN LA?

Active ingredient: methylphenidate HCl

Inactive ingredients: ammonio methacrylate copolymer, black iron oxide (10 and 40 mg capsules only), gelatin,

methacrylic acid copolymer, polyethylene glycol, red iron oxide (10 and 40 mg capsules only), sugar spheres, talc,

titanium dioxide, triethyl citrate, and yellow iron oxide (10, 30, and 40 mg capsules).

RITALIN LA® is a trademark of Novartis AG.

Distributed by:

Novartis Pharmaceuticals Corporation East Hanover, New Jersey 07936

© Novartis

For more information, call 1-888-669-6682.

This Medication Guide has been approved by the U.S. Food and Drug Administration. Revised: 09/2025

PRINCIPAL DISPLAY PANEL

NDC 0078-0424-05 Rx only

Ritalin LA®
(methylphenidate HCl)
extended-release capsules

10 mg

100 capsules

Dispense with Medication
Guide attached or provided
separately.

NOVARTIS

PRINCIPAL DISPLAY PANEL

NDC 0078-0370-05 Rx only

Ritalin LA®
(methylphenidate HCl)
extended-release capsules

20 mg

100 capsules

Dispense with Medication
Guide attached or provided
separately.

NOVARTIS

PRINCIPAL DISPLAY PANEL

NDC 0078-0371-05 Rx only

Ritalin LA®
(methylphenidate HCl)
extended-release capsules

30 mg

100 capsules

Dispense with Medication
Guide attached or provided
separately.

NOVARTIS

PRINCIPAL DISPLAY PANEL

NDC 0078-0372-05 Rx only

Ritalin LA®
(methylphenidate HCl)
extended-release capsules

40 mg

100 capsules

Dispense with Medication
Guide attached or provided
separately.

NOVARTIS